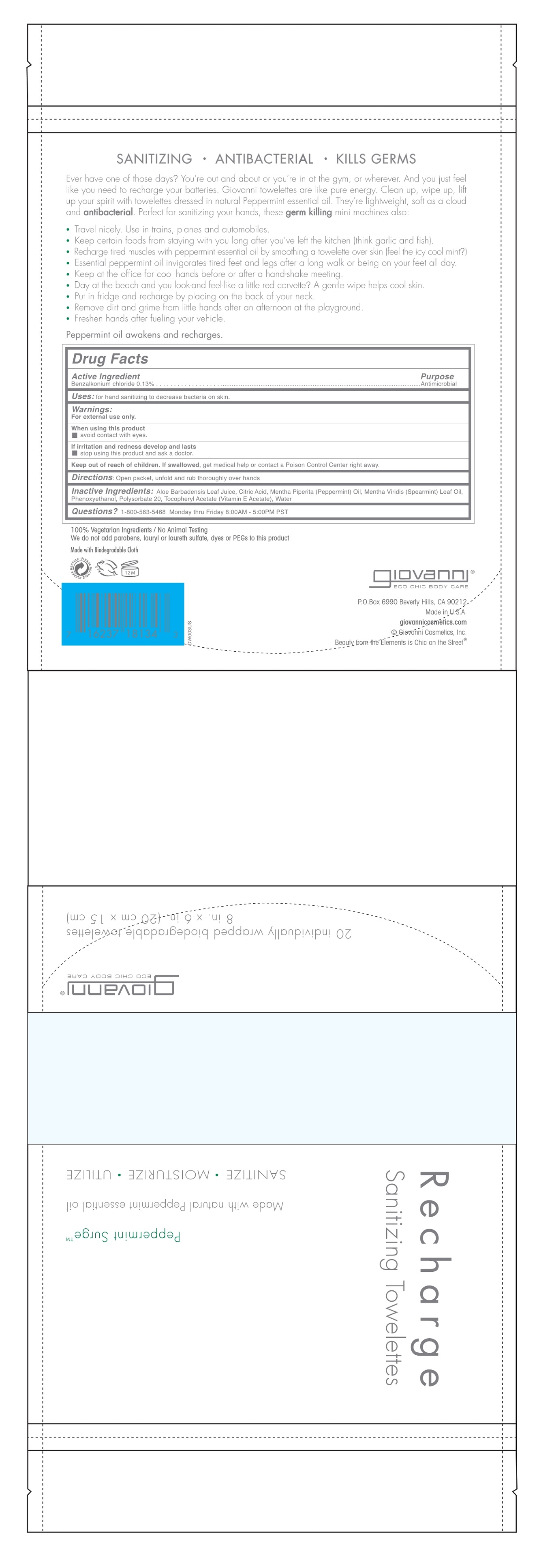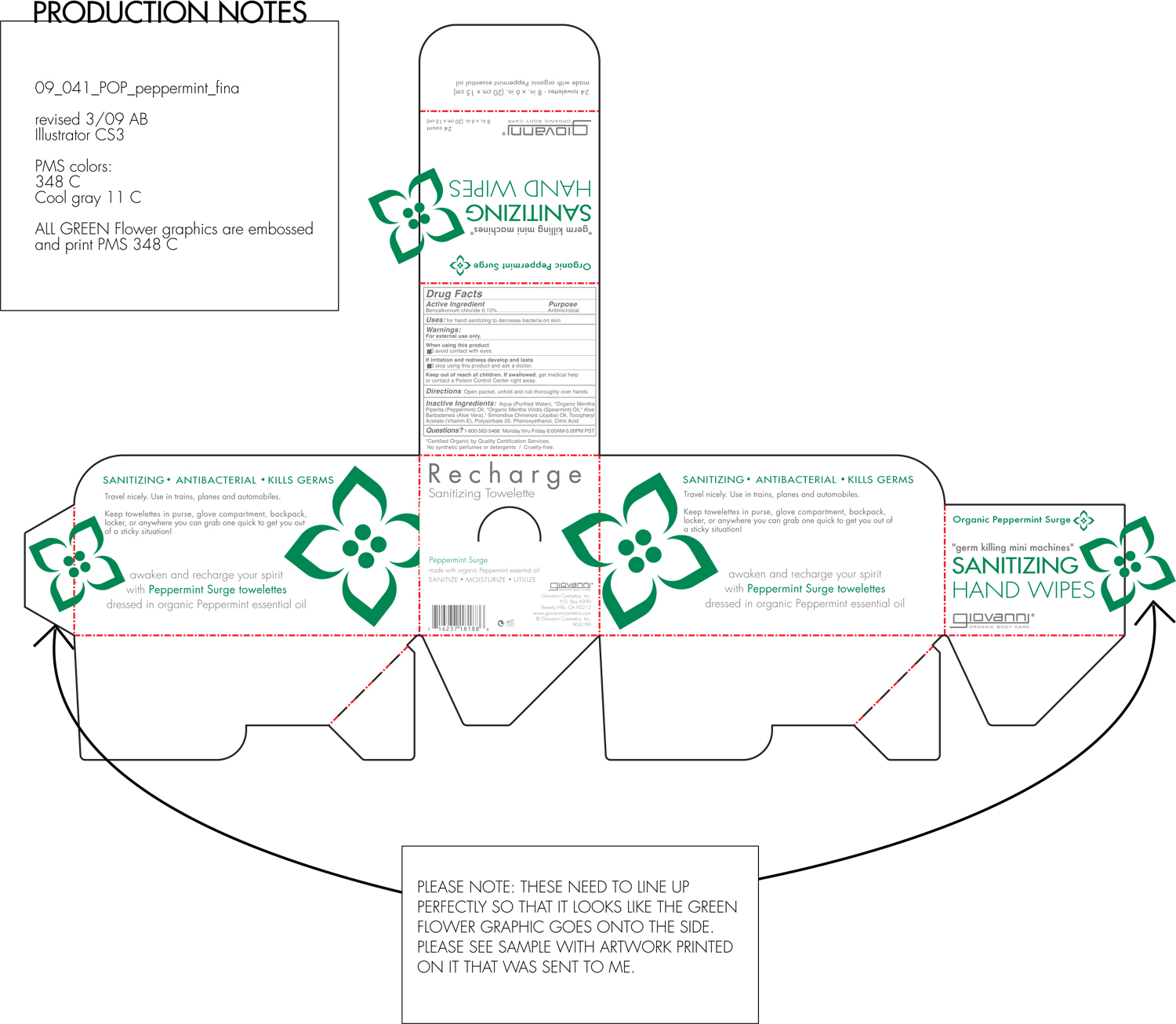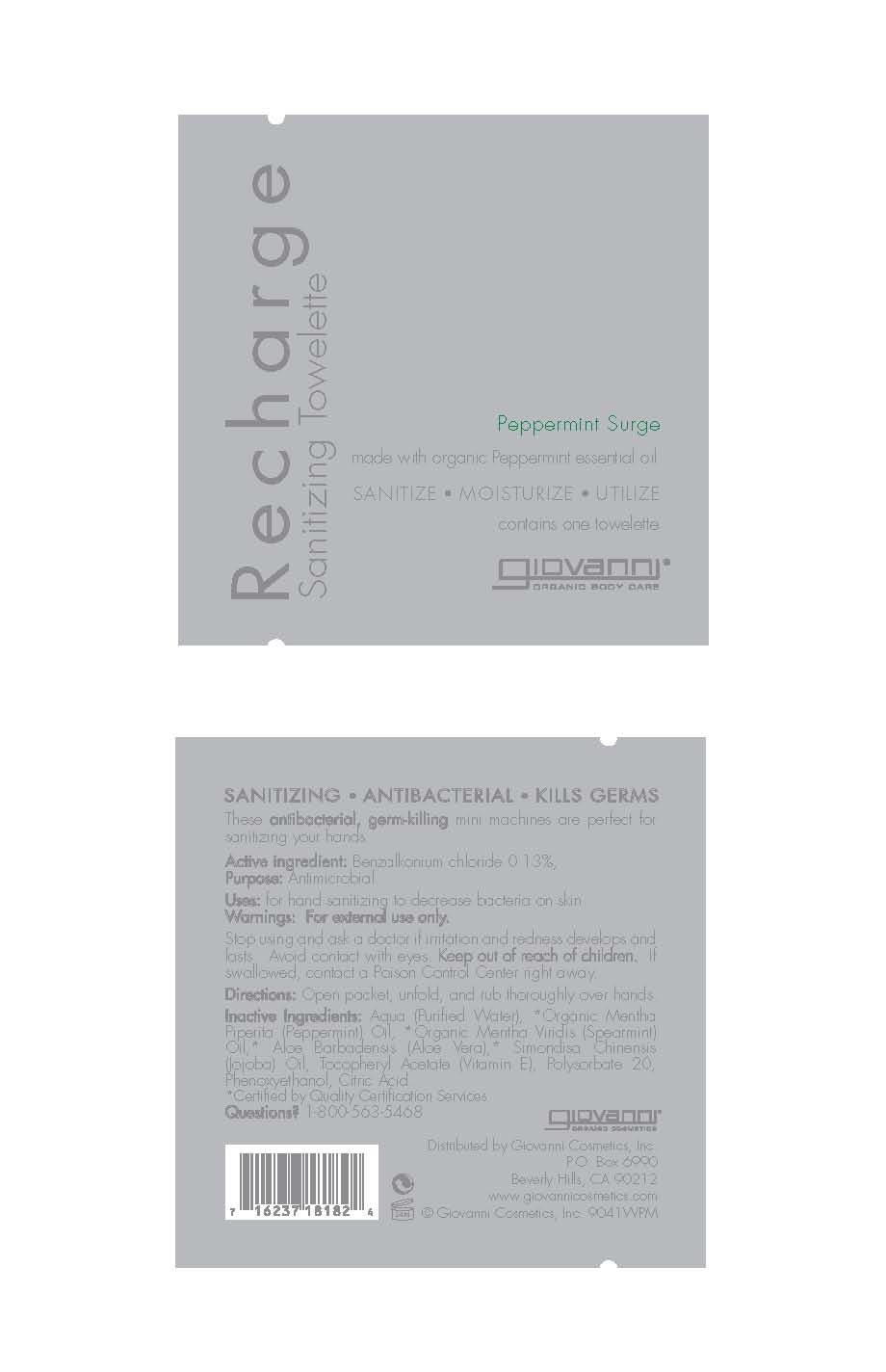 DRUG LABEL: Recharge Sanitizing Towlette
NDC: 45942-1630 | Form: LIQUID
Manufacturer: GIOVANNI COSMETICS INC
Category: otc | Type: HUMAN OTC DRUG LABEL
Date: 20180129

ACTIVE INGREDIENTS: BENZALKONIUM CHLORIDE 0.13 g/100 mL
INACTIVE INGREDIENTS: Water; Peppermint oil; Polysorbate 20; Spearmint Oil; Aloe Vera Leaf; Phenoxyethanol; ANHYDROUS CITRIC ACID; .ALPHA.-TOCOPHEROL ACETATE, DL-

Recharge Packaging

Active Ingredient

Benzalkonium Chloride 0.13%

Purpose

Antimicrobial

Uses

For hand sanitizing to decrease bacteria on skin.

Questions

Questions? 1-800-563-5458 Monday thru Friday 8:00 AM - 5:00 PM PST

Keep Out Of Reach Of Children

If swallowed, get medical help or contact a Poison Control Center right away.

Directions

Open packet, unfold and rub thoroughly over hands.

Warnings

For external use only.
When using this product avoid contact with eyes.
If irritation and redness develop and lasts, stop using this product and ask a doctor.

Inactive Ingredients

Aloe Barbadensis Leaf Juice, Citric Acid, Mentha Piperita (Peppermint) Oil, Mentha Virdis (Spearmint) Leaf Oil, Phenoxyethanol, Polysorbate 20, Tocopheryl Acetate (Vitamin E Acetate), Water

Uses

For hand sanitizing to decrease bacteria on the skin.

PACKAGE LABEL

Recharge Sanitizing Towelette

Peppermint Surge

Made with organic peppermint essential oil